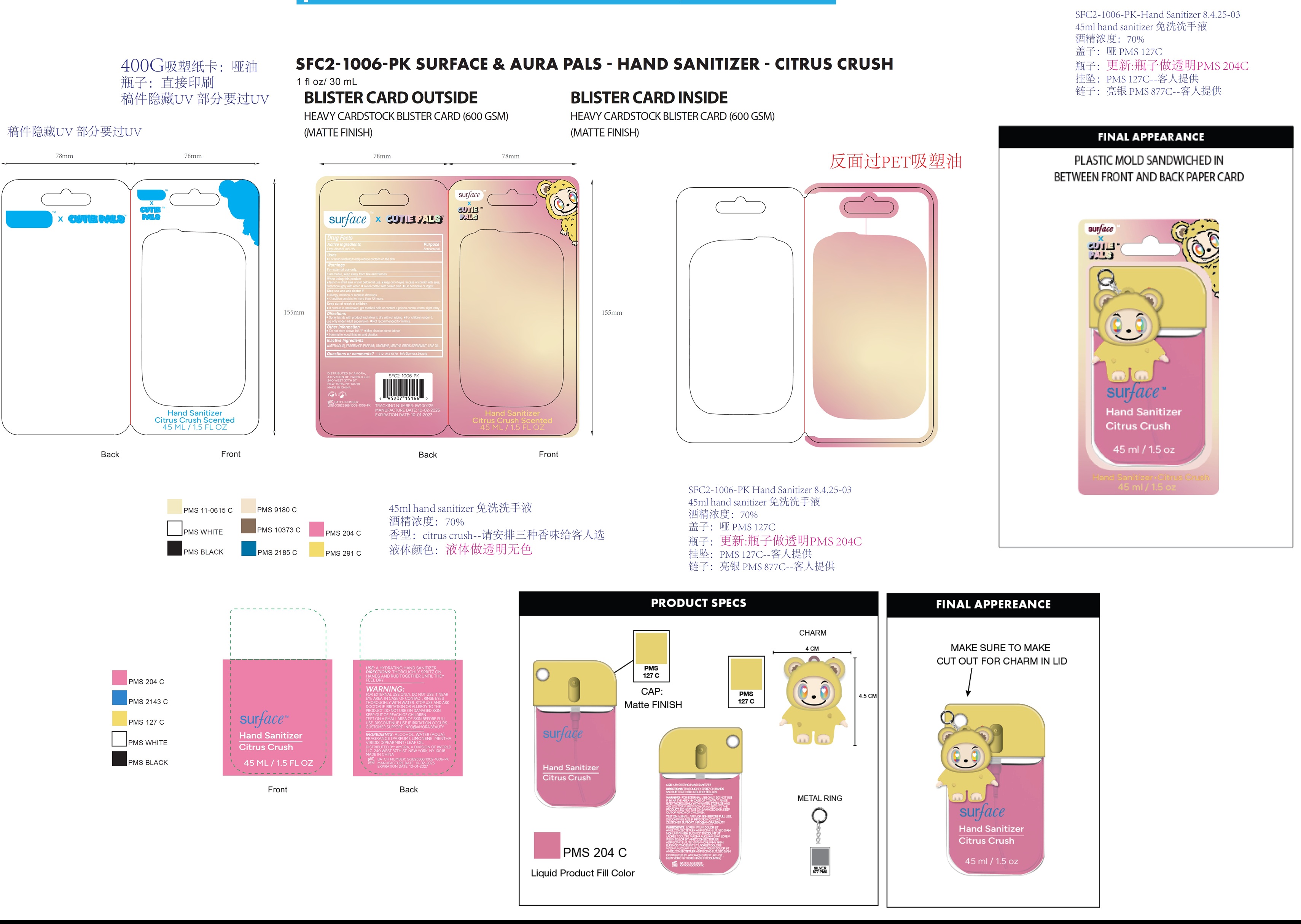 DRUG LABEL: Surface x Cutie Pals Hand Sanitizer Citrus Crush
NDC: 85179-010 | Form: LIQUID
Manufacturer: I World LLC
Category: otc | Type: HUMAN OTC DRUG LABEL
Date: 20251121

ACTIVE INGREDIENTS: ALCOHOL 70 mL/100 mL
INACTIVE INGREDIENTS: WATER; LIMONENE, (+)-; SPEARMINT OIL

Surface x Cutie Pals Hand Sanitizer, Citrus Crush

Active ingredients

Ethyl Alcohol 70% v/v

Purpose

Antibacterial

Uses

- For hand-washing to help reduce bacteria on the skin.

Warnings

For external use only.

Flammable, keep away from fire and flames

When using this product

- test on a small area of skin before full use. keep out of eyes. In case of contact with eyes, flush thoroughly with water. Avoid contact with broken skin. Do not inhale or ingest.

Stop use and ask doctor if

- allergy, irritation or redness develops.
- Condition persists for more than 72 hours.

Keep out of reach of children.

- If product is swallowed, get medical help or contact a poison control center right away.

Directions

• Spray hands with product and allow to dry without wiping. • For children under 6, use only under adult supervision. • Not recommended for infants.

Other information

• Do not store above 105 °F • May discolor some fabrics
• Harmful to wood finishes and plastics

Inactive ingredients

WATER (AQUA), FRAGRANCE (PARFUM), LIMONENE, MENTHA VIRIDIS (SPEARMINT) LEAF OIL.

Questions or comments?

1-212- 244-5170 info@amora.beauty